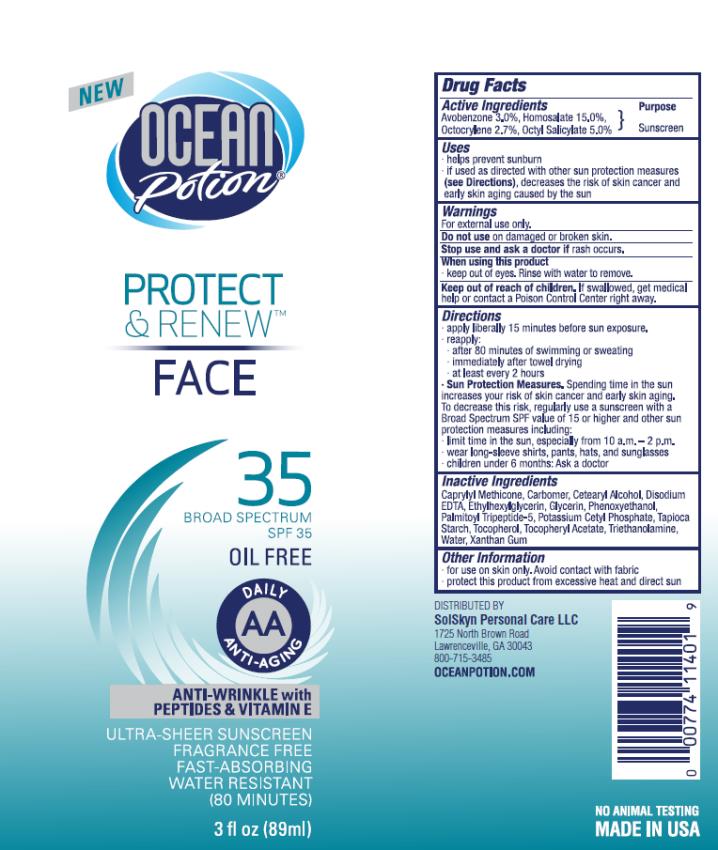 DRUG LABEL: OP Protect and Renew Face SPF 35
NDC: 70281-211 | Form: LOTION
Manufacturer: SolSkyn Personal Care LLC
Category: otc | Type: HUMAN OTC DRUG LABEL
Date: 20180215

ACTIVE INGREDIENTS: AVOBENZONE 3 g/100 g; HOMOSALATE 15 g/100 g; OCTOCRYLENE 2.7 g/100 g; OCTISALATE 5 g/100 g
INACTIVE INGREDIENTS: CAPRYLYL TRISILOXANE; CARBOXYPOLYMETHYLENE; CETOSTEARYL ALCOHOL; EDETATE DISODIUM ANHYDROUS; ETHYLHEXYLGLYCERIN; GLYCERIN; PHENOXYETHANOL; PALMITOYL TRIPEPTIDE-5; POTASSIUM CETYL PHOSPHATE; STARCH, TAPIOCA; TOCOPHEROL; ALPHA-TOCOPHEROL ACETATE; TROLAMINE; WATER; XANTHAN GUM

OP-SPF35 3oz Protect Renew Face

OP Protect & Renew Face SPF 35

Active Ingredients

Avobenzone 3.0%

Active Ingredients

Homosalate 15.0%

Active Ingredients

Octocrylene 2.7%

Active Ingredients

Octyl Salicylate 5.0%

Purpose

Sunscreen

Uses:

• Helps prevent sunburn

• If used as directed with other sun protection measures (see Directions), decreases the risk of skin cancer and early skin aging caused by the sun

Warnings:

• For external use only.

• Keep out of reach of children.

If swallowed, get medical help or contact a Poison Control Center right away.

Directions

• Apply liberally 15 minutes before sun exposure.

• Re-apply:

• after 80 minutes of swimming or sweating

• immediately after towel drying

• at least every two hours

• Sun Protection Measures. Spending time in the sun increases your risk of skin cancer and early skin aging. To decrease this risk, regularly use a sunscreen with a Broad Spectrum SPF value of 15 or higher and other sun protection measures including:

• limit time in the sun, especially from 10 a.m.-2 p.m.

• wear long-sleeved shirts, pants, hats and sunglasses

• Children under 6 months: ask a doctor.

Inactive ingredients

Caprylyl Methicone, Carbomer, Cetearyl Alcohol, Disodium EDTA, Ethylhexlglycerin, Glycerin, Phenoxyethanol, Palmitoyl Tripeptide-5, Potassium Cetyl Phosphate, Tapioca Starch, Tocopherol, Tocopherol Acetate, Triethanolamine, Water, Xanthan Gum

Other information:

• For use on skin only. Avoid contact with fabric.

• Protect this product from excessive heat and direct sun.

PRINCIPAL DISPLAY PANEL

Ocean Potion
Protect
& Renew
face
SPF 35
3 fl oz (89ml)